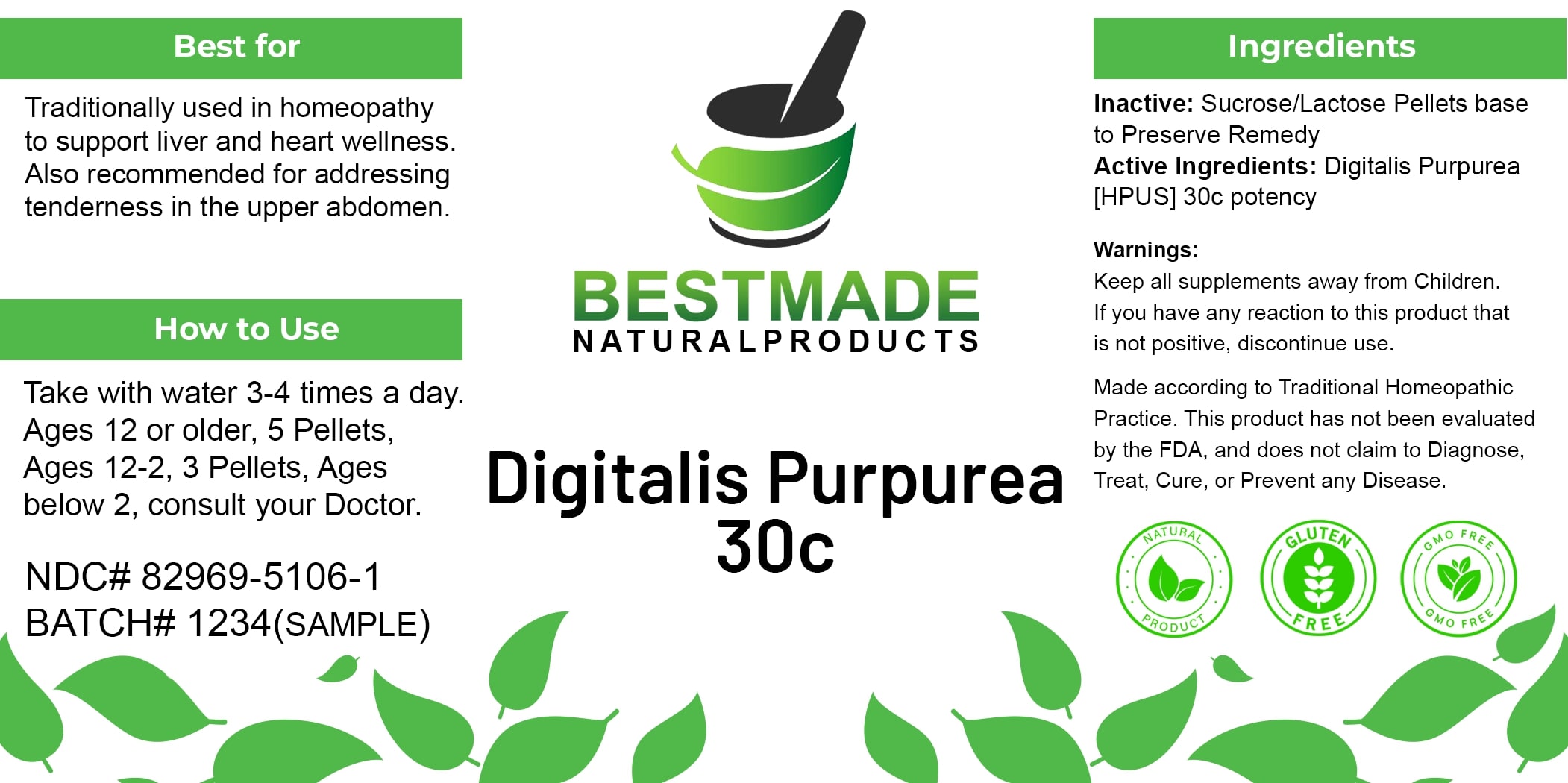 DRUG LABEL: Bestmade Natural Products Digitalis Purpurea
NDC: 82969-5106 | Form: TABLET, SOLUBLE
Manufacturer: Bestmade Natural Products
Category: homeopathic | Type: HUMAN OTC DRUG LABEL
Date: 20241219

ACTIVE INGREDIENTS: DIGITALIS 30 [hp_C]/30 [hp_C]
INACTIVE INGREDIENTS: LACTOSE 30 [hp_C]/30 [hp_C]; SUCROSE 30 [hp_C]/30 [hp_C]

Digitalis Purpurea 30c

DOSAGE AND ADMINISTRATION

Take with water 3-4 times a day
Ages 12 or older, 5 Pellets, Ages 12-2, 3 Pellets, Ages below 2, consult your Doctor.

INDICATIONS AND USAGE

Best for

Traditionally used in homeopathy to support liver and heart wellness. Also recommended for addressing tenderness in the upper abdomen.

INACTIVE INGREDIENT

Ingredients

Inactive: Sucrose/Lactose Pellets base to Preserve Remedy

Active Ingredients: Digitalis Purpurea [HPUS] 30c potency

Warnings:

Keep all supplements away from Children.

If you have any reaction to this product that is not positive, discontinue use.

Made according to Traditional Homeopathic Practice. This product has not been evaluated by the FDA, and does not claim to Diagnose, Treat, Cure, or Prevent any Disease.

PURPOSE

Best for

Traditionally used in homeopathy to support liver and heart wellness. Also recommended for addressing tenderness in the upper abdomen.

Warnings:

Keep all supplements away from Children.

If you have any reaction to this product that is not positive, discontinue use.

Made according to Traditional Homeopathic Practice. This product has not been evaluated by the FDA, and does not claim to Diagnose, Treat, Cure, or Prevent any Disease.

Entire package label